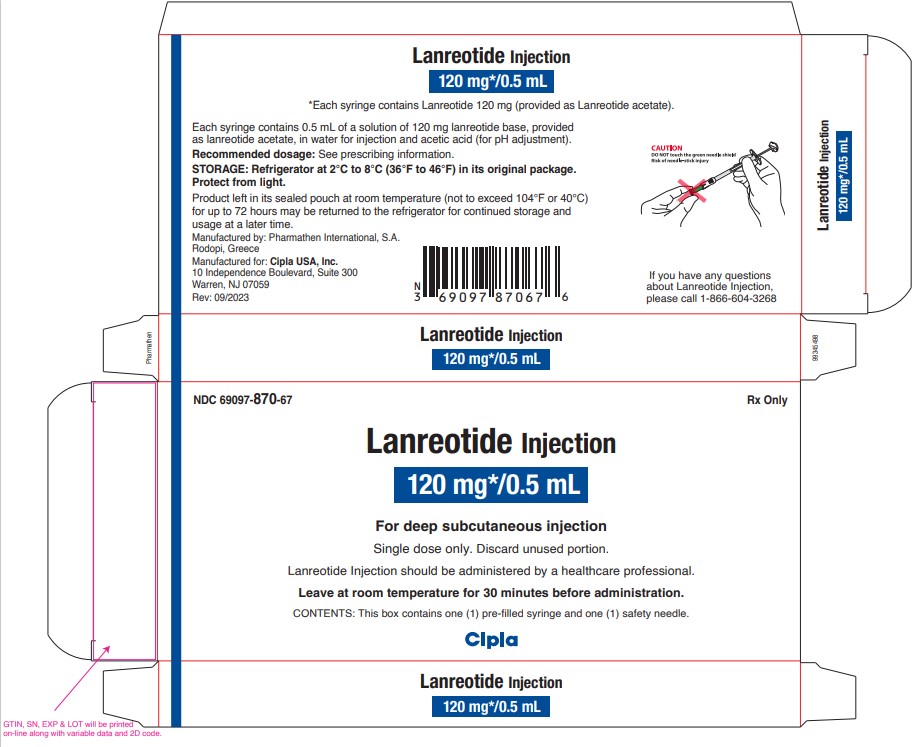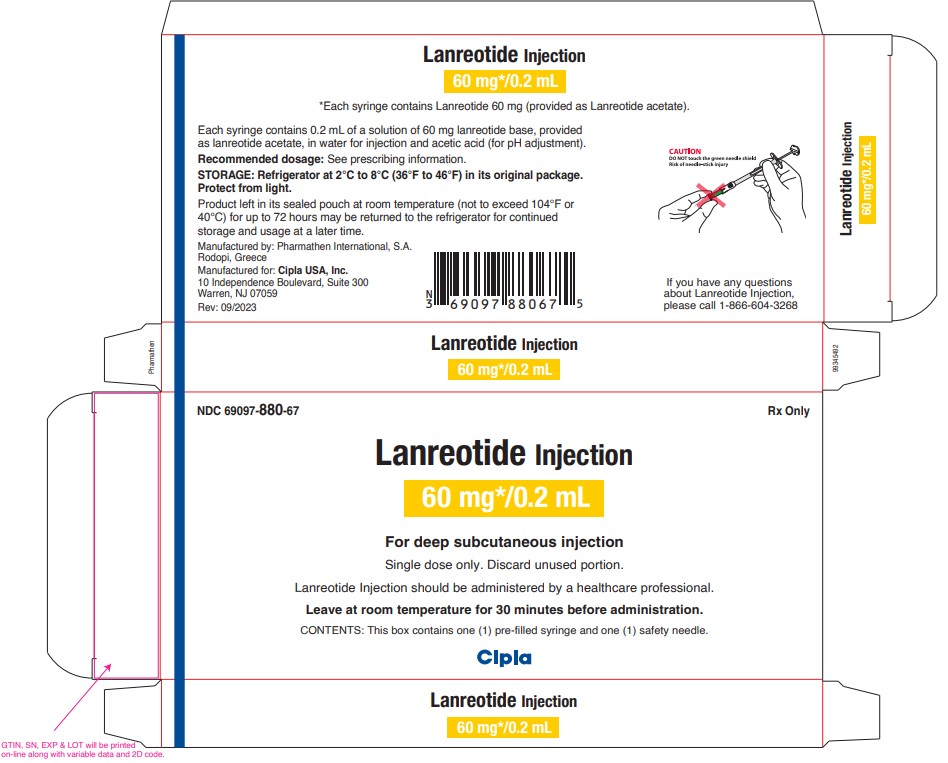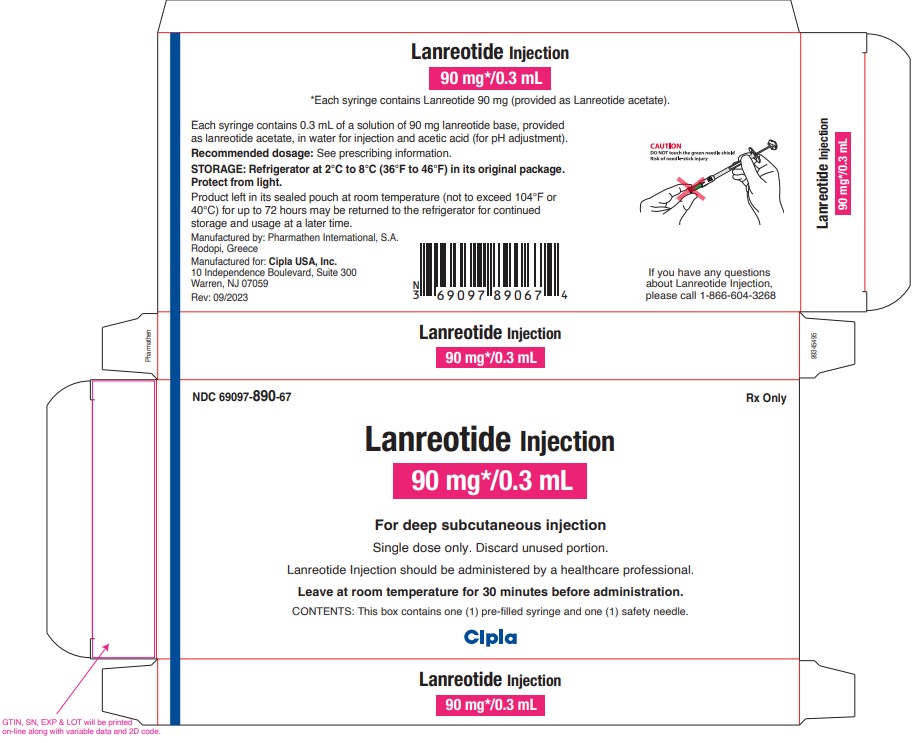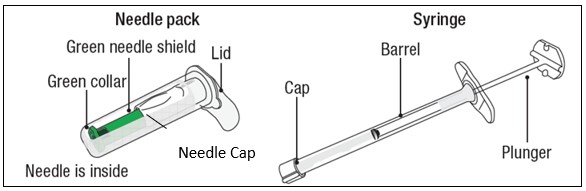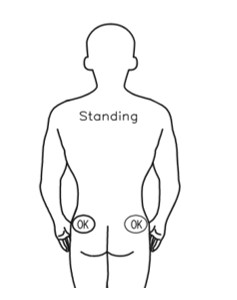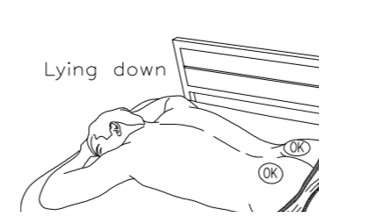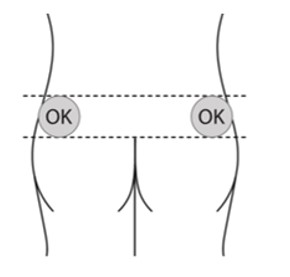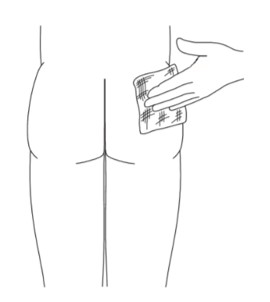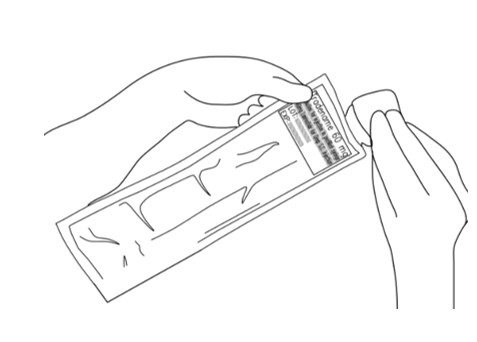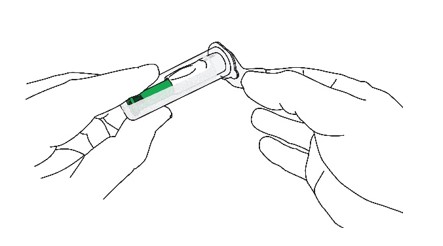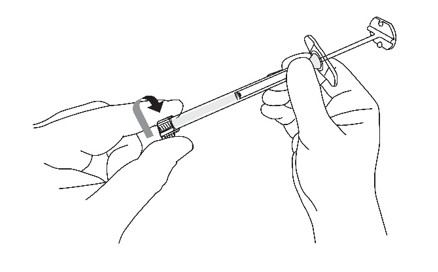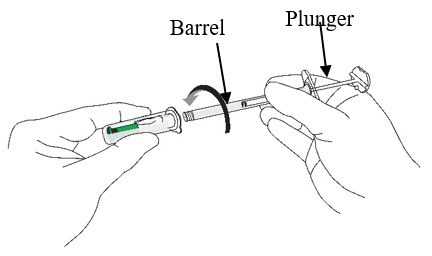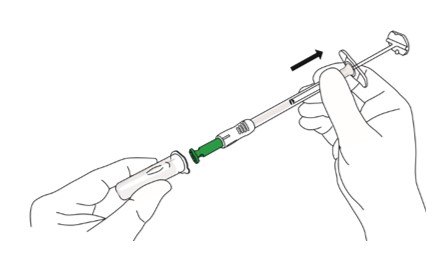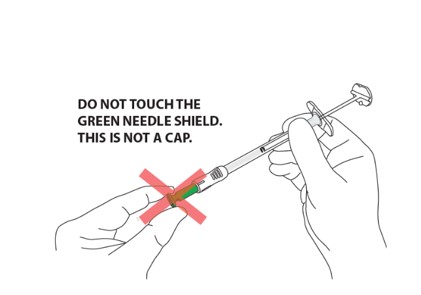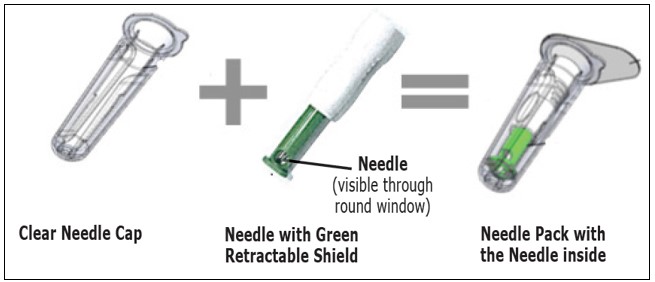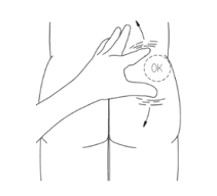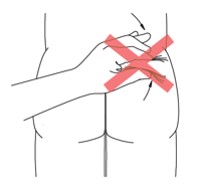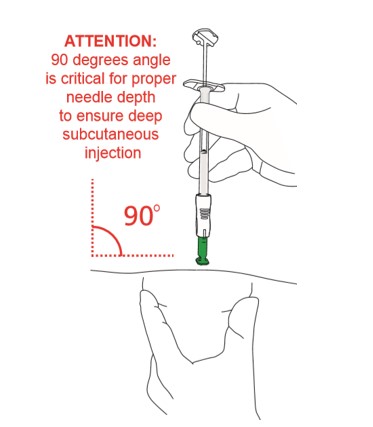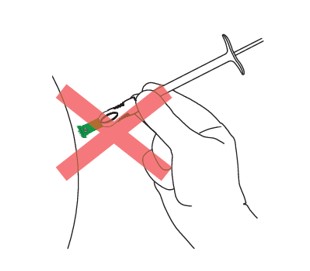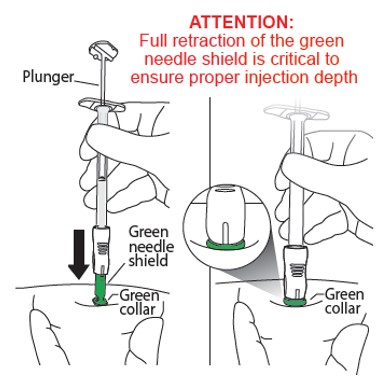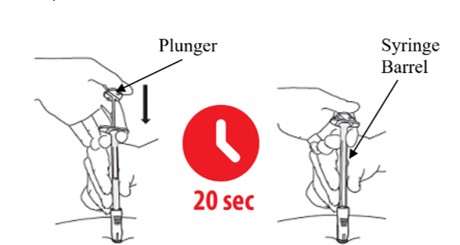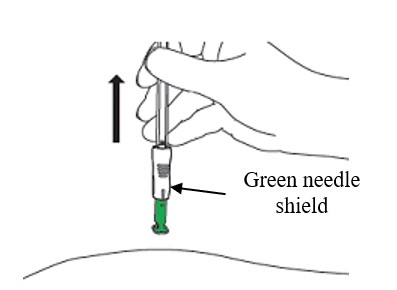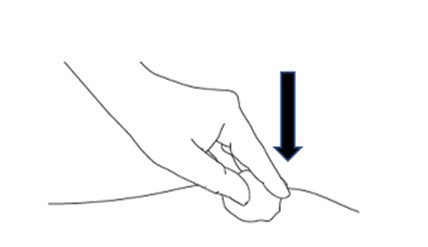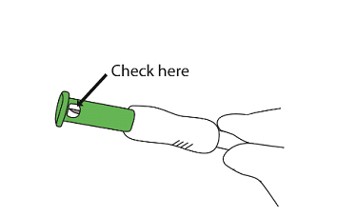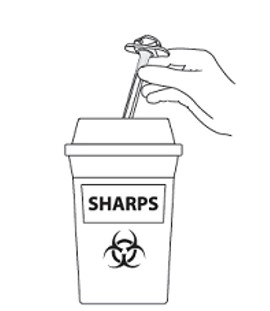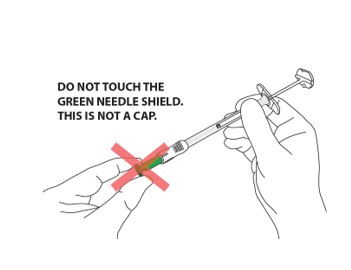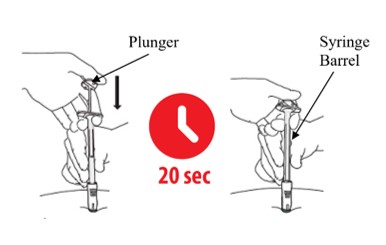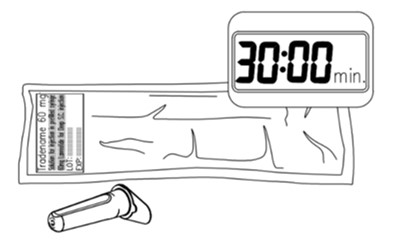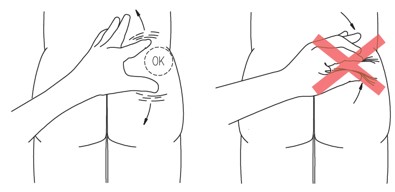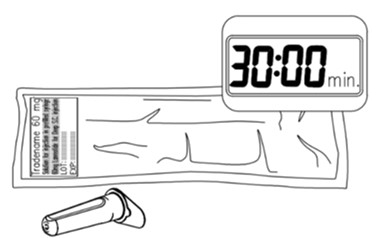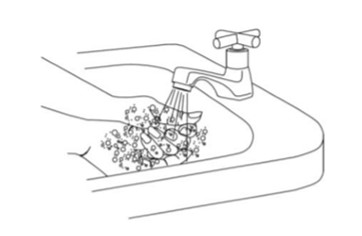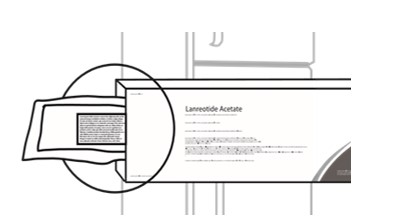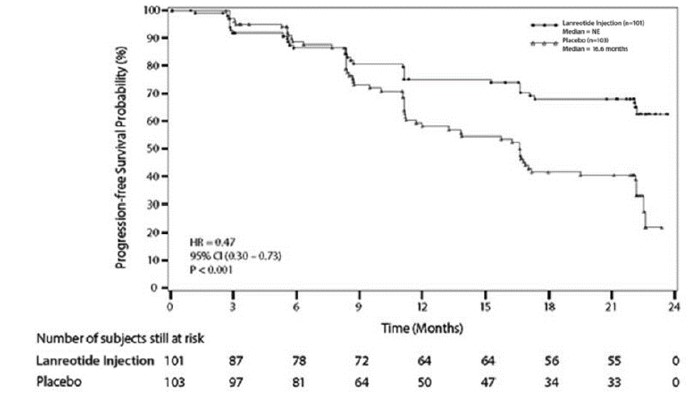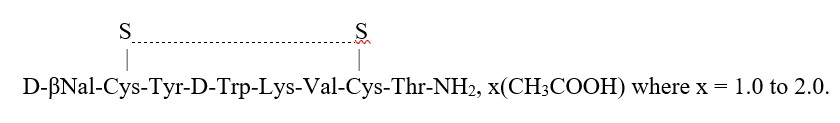 DRUG LABEL: Lanreotide Acetate
NDC: 69097-880 | Form: INJECTION
Manufacturer: Cipla USA Inc.
Category: prescription | Type: HUMAN PRESCRIPTION DRUG LABEL
Date: 20240901

ACTIVE INGREDIENTS: LANREOTIDE ACETATE 60 mg/0.2 mL

HIGHLIGHTS OF PRESCRIBING INFORMATION

These highlights do not include all the information needed to use LANREOTIDE INJECTION safely and effectively. See full prescribing information for LANREOTIDE INJECTION.
LANREOTIDE injection, for subcutaneous use
Initial U.S. Approval: 2007

RECENT MAJOR CHANGES

Indications and Usage, Carcinoid Syndrome (1.3) 09/2024

Dosage and Administration (2.1) 09/2024

Warnings and Precautions, Steatorrhea and Malabsorption of Dietary

Fats (5.6) 07/2024

1 INDICATIONS AND USAGE

Lanreotide Injection is a somatostatin analog indicated for:

- the long-term treatment of acromegalic patients who have had an inadequate response to or cannot be treated with surgery and/or radiotherapy. (1.1)
- the treatment of adult patients with unresectable, well- or moderately- differentiated, locally advanced or metastatic gastroenteropancreatic neuroendocrine tumors (GEP-NETs) to improve progression-free survival. (1.2)
- the treatment of adults with carcinoid syndrome; when used, it reduces the frequency of short-acting somatostatin analog rescue therapy. (1.3)

2 DOSAGE AND ADMINISTRATION

Administration (2.1):

- For deep subcutaneous injection only.
- Intended for administration by a healthcare provider.
- Administer in the superior external quadrant of the buttock.
- Alternate injection sites.

Recommended Dosage (2.1)

- Acromegaly: 90 mg every 4 weeks for 3 months. Adjust thereafter based on GH and/or IGF-1 levels. See full prescribing information for titration regimen.
- GEP-NETs: 120 mg every 4 weeks.
- Carcinoid Syndrome: 120 mg every 4 weeks. If patients are already being treated with Lanreotide Injection for GEP-NET, do not administer an additional dose for carcinoid syndrome.

Dosage Adjustment:

- See full prescribing information for dosage adjustment in patients with acromegaly and renal or hepatic impairment. (2.2, 2.3)

3 DOSAGE FORMS AND STRENGTHS

Injection: 60 mg/0.2 mL, 90 mg/0.3 mL, and 120 mg/0.5 mL of lanreotide in single-dose prefilled syringes (3)

4 CONTRAINDICATIONS

Hypersensitivity to lanreotide. (4)

5 WARNINGS AND PRECAUTIONS

- Cholelithiasis and Complications of Cholelithiasis: Monitor periodically. Discontinue if complications of cholthiasis are suspected. Gallstones may occur; consider periodic monitoring. (5.1)
- Hyperglycemia and Hypoglycemia: Glucose monitoring is recommended and antidiabetic treatment adjusted accordingly. (5.2, 7.1)
- Cardiovascular Abnormalities: Decrease in heart rate may occur. Use with caution in at-risk patients. (5.3)
- Thyroid Function Abnormalities: Decreases in thyroid function may occur; perform tests where clinically indicated. (5.4)
- Steatorrhea and Malabsorption of Dietary Fats: New onset steatorrhea, stool discoloration, loose stools, abdominal bloating, and weight loss may occur. If new occurrence or worsening of these symptoms are reported, evaluate for potential pancreatic exocrine insufficiency. (5.6)

6 ADVERSE REACTIONS

Most common adverse reactions are:

- Acromegaly : (>5%): diarrhea, cholelithiasis, abdominal pain, nausea and injection site reactions. (6.1)
- GEP-NET : (>10%): abdominal pain, musculoskeletal pain, vomiting, headache, injection site reaction, hyperglycemia, hypertension, and cholelithiasis. (6.1)
- Carcinoid Syndrome: (≥5% and at least 5% greater than placebo): headache, dizziness and muscle spasm. (6.1)

To report SUSPECTED ADVERSE REACTIONS, contact Cipla Ltd. Inc. at 1-866-604-3268 or FDA at 1-800-FDA-1088 or www.fda.gov/medwatch

7 DRUG INTERACTIONS

- Cyclosporine: Lanreotide Injection may decrease the absorption of cyclosporine. Dosage adjustment of cyclosporine may be needed. (7.2)
- Bromocriptine: Lanreotide Injection may increase the absorption of bromocriptine. (7.3)
- Bradycardia-Inducing Drugs (e.g., beta-blockers): Lanreotide Injection may decrease heart rate. Dosage adjustment of the coadministered drug may be necessary. (7.3)

8 USE IN SPECIFIC POPULATIONS

Lactation: Advise women not to breastfeed during treatment and for 6 months after the last dose. (8.2)

FULL PRESCRIBING INFORMATION

1 INDICATIONS AND USAGE

1.1 Acromegaly

Lanreotide Injection is indicated for the long-term treatment of acromegalic patients who have had an inadequate response to surgery and/or radiotherapy, or for whom surgery and/or radiotherapy is not an option.

The goal of treatment in acromegaly is to reduce growth hormone (GH) and insulin growth factor-1 (IGF-1) levels to normal.

1.2 Gastroenteropancreatic Neuroendocrine Tumors

Lanreotide Injection is indicated for the treatment of adult patients with unresectable, well or moderately differentiated, locally advanced or metastatic gastroenteropancreatic neuroendocrine tumors (GEP-NETs) to improve progression-free survival.

1.3 Carcinoid Syndrome

Lanreotide Injection is indicated for the treatment of adults with carcinoid syndrome; when used, it reduces the frequency of short-acting somatostatin analog rescue therapy.

2 DOSAGE AND ADMINISTRATION

2.1 Recommended Dosage

Acromegaly

The recommended starting dosage of Lanreotide Injection is 90 mg given via the deep subcutaneous route, at 4-week intervals for 3 months.

After 3 months, the Lanreotide injection dosage may be adjusted as follows:

- GH greater than 1 ng/mL to less than or equal to 2.5 ng/mL, IGF-1 normal, and clinical symptoms controlled: maintain dosage at 90 mg every 4 weeks.
- GH greater than 2.5 ng/mL, IGF-1 elevated, and/or clinical symptoms uncontrolled: increase dosage to 120 mg every 4 weeks.
- GH less than or equal to 1 ng/mL, IGF-1 normal, and clinical symptoms controlled: reduce dosage to 60 mg every 4 weeks.

Thereafter, the dosage should be adjusted according to the response of the patient as judged by a reduction in serum GH and/or IGF-1 levels; and/or changes in symptoms of acromegaly.

Patients who are controlled on Lanreotide Injection 60 or 90 mg may be considered for an extended dosing interval of Lanreotide Injection 120 mg every 6 or 8 weeks. GH and IGF-1 levels should be obtained 6 weeks after this change in dosing regimen to evaluate persistence of patient response.

Continued monitoring of patient response with dosage adjustments for biochemical and clinical symptom control, as necessary, is recommended.

Gastroenteropancreatic Neuroendocrine Tumors (GEP-NETs)

The recommended dosage of Lanreotide Injection is 120 mg administered every 4 weeks by deep subcutaneous injection.

Carcinoid Syndrome

The recommended dosage of Lanreotide Injection is 120 mg administered every 4 weeks by deep subcutaneous injection. If patients are already being treated with Lanreotide Injection for GEP-NETs, do not administer an additional dose for the treatment of carcinoid syndrome.

2.2 Dosage Adjustment in Renal Impairment

Acromegaly

The recommended starting dosage of Lanreotide Injection in acromegalic patients with moderate or severe renal impairment (creatinine clearance (CLcr) less than 60 mL/min) is 60 mg via the deep subcutaneous route at 4-week intervals for 3 months followed by dosage adjustment [see Dosage and Administration (2.1), Use in Specific Populations (8.6)].

2.3 Dosage Adjustment in Hepatic Impairment

Acromegaly

The recommended starting dosage of Lanreotide Injection in acromegalic patients with moderate or severe hepatic impairment (Child-Pugh Class B or C) is 60 mg via the deep subcutaneous route at 4-week intervals for 3 months followed by dosage adjustment [see Dosage and Administration (2.1), Use in Specific Populations (8.7)].

2.4 Important Preparation and Administration Instructions

The following instructions explain how to inject Lanreotide Injection:

1. Read all instructions carefully before starting the injection. Follow this procedure exactly, as it may differ from your past experience.
2. This is a single-dose pre-filled syringe with a single-use safety needle with a green needle shield (that cannot be removed) in a clear needle cap.
3. ALL the medication must be injected SLOWLY over 20 seconds during the use.
4. If you drop or damage the device in any way, please call 1-866-604-3268.

Figure 1

The box includes the following items:

- Sterile needle pack containing Sterile needle
- Sterile Laminated pouch with sterile syringe pre-filled with LANREOTIDE INJECTION
- Instructions for Use Leaflet
- Prescribing Information Leaflet

CAUTION

- NEVER TOUCH OR TRY TO OPEN THE GREEN NEEDLE SHIELD throughout the course of operation of the device.
- Green needle shield is NOT a removable cap or cover for the needle.
- Green needle shield will automatically activate once the injection is complete.
- Green needle shield is a self-operating safety lock mechanism.
- Needle is fully covered by green needle shield.
- Needle is visible only through a small window in the green needle shield.

- Inject medication slowly over 20 seconds.
- DO NOT rush the injection.

- Remove box from refrigerator 30 minutes prior to injecting.
- Product left in its sealed pouch at room temperature (not to exceed 104°F or 40°C) for up to 72 hours may be returned to the refrigerator for continued storage and usage at a later time.

- Stretch out the skin around injection site to make it flat and tight using your thumb and index finger.
- DO NOT pinch the skin around injection site.

A. BEFORE YOU START

Figure 2

A1. Remove LANREOTIDE INJECTION from the refrigerator 30 minutes prior to injecting (Figure 2). Do not open the sterile pouch yet.

Note: Product left in its sealed pouch at room temperature (not to exceed 104° F or 40 °C) for up to 72 hours may be returned to the refrigerator for continued storage and use at a later time.

Figure 3

A2. Wash your hands with soap and dry your hands thoroughly before starting (Figure 3).

Follow the doctor or institution’s policy on the use of surgical gloves during the procedure

Figure 4

A3. Before opening the sterile pouch, confirm that it is intact, and that the medication has not expired. The Syringe is sterile only if the pouch is sealed and undamaged. Do not use if the pouch is opened, tampered with or damaged. The expiry date is printed on the outer carton and the pouch - Do not use if the medication has expired. (Figure 4).

Or

Figure 5

A4. Make sure there is a clean surface for preparation.

Find a clean, comfortable area for the patient to relax during procedure (Figure 5).

It's important that the patient remains as still as possible during the injection.

Figure 6

A5. Choose injection site - the sites are upper outer areas of the buttock as shown below

It is very important that you only inject in one of the areas marked OK in the picture (Figure 6).

Alternate the injection site between the right and left side each time an injection of LANREOTIDE INJECTION is administered.

Figure 7

A6. Prepare the injection site by cleaning it with alcohol wipes (Figure 7).

Figure 8

A7. Tear open the sterile pouch and take out the sterile pre-filled syringe (Figure 8).

B. PREPARE THE SYRINGE

Figure 9

B1: Open the sterile needle cap (Figure 9)

- The needle is sterile only if the needle cap is sealed and undamaged. Do not use if the needle cap is opened, tampered with or damaged.
- Hold the clear needle cap and pull the lid off.
- DO NOT TOUCH THE OPEN END OF THE NEEDLE CAP TO MAINTAIN STERILITY.

Figure 10

B2: Remove the cap from the sterile syringe (Figure 10)

- With one hand, hold the syringe barrel steady (not the plunger).
- With the other hand, remove the cap by twisting it.

B3: Prepare the assembly (Figure 11)

Figure 11

- Hold the needle cap with one hand and the syringe barrel (not the plunger) with the other
- Carefully insert the open end of the syringe into the open end of the needle cap
- Twist the syringe barrel clockwise until it is tight to make sure that the syringe is well connected to the safety needle.
- ENSURE THAT BOTH PARTS OF THE DEVICE (SYRINGE AND NEEDLE) ARE COMPLETELY CONNECTED.

The assembly is fully locked when you cannot turn it any further.

B4: Remove the needle from the needle cap

Figure 12

- Hold the syringe barrel (not the plunger).
- Pull the needle straight out from the needle cap without twisting or turning (Figure 12).

Figure 13

CAUTION: NEVER TOUCH THE GREEN NEEDLE SHIELD. THERE IS A RISK OF NEEDLE STICK INJURY. (Figure 13)

- Green needle shield is a self-operating safety lock mechanism and is not a removable cover or cap for the needle. It will activate once the injection is complete.
- The needle is fully covered by the green shield and is visible only through the small round window at the end of the shield.

C.PERFORM INJECTION

C1: Position the syringe assembly

Figure 14

- Stretch out the skin around the injection site to make it flat and tight using your thumb and index finger. (Figure 14)

Figure 15

DO NOT pinch the skin (Figure 15)

Figure 16

- Hold the assembly by the lower part of the syringe barrel (not the plunger) with your other hand.
- Position the syringe assembly at a 90-degree angle to the skin. The green collar at the bottom of the green shield should be perpendicular to the injection site (Figures 16 and 17)

Figure 17

C2: Insert the needle (Figure 18)

Figure 18

- Holding the skin flat and tight, push the syringe assembly firmly into the skin.
- Do NOT pinch the skin.
- Keep pushing until you reach a “hard stop” and only the green collar at the end of the green needle shield remains visible.
- Do NOT push the plunger yet.
- DO NOT aspirate.
- Keep pressing against the skin.
- During this step you should not see the needle.

C3: Push the top of the plunger (Figure 19)

Figure 19

- Keep holding your hand on the syringe barrel to maintain a 90-degree angle throughout the injection.
- While keeping the syringe pressed against the skin, slowly press down the plunger. You may want to use both hands while applying pressure during the injection of drug.
- Continue slowly pushing the plunger over 20 seconds until the Plunger top touches the syringe end .
- DO NOT rush the injection. The medication is thicker and harder to push than you might expect. Pushing the plunger too fast may cause discomfort to the patient.
- While depressing the plunger, slowly count to 20 and CONTINUE STEADY PRESSURE on the plunger. You may find it helpful to say:

a “1 one-thousand”

b “2 one-thousand”

c “3 one-thousand” up to “20 one-thousand”

- During this step, as the needle is lowering, the green needle shield will retract. You should only see the green collar of the green needle shield.
- During this step you should not see the needle.

D. REMOVE AND THROW AWAY THE SYRINGE ASSEMBLY

Figure 20

D1: Remove from the skin (Figure 20)

- Lift the syringe straight up and away from the body.
- The green needle shield will return to its original position and will fully cover the needle.

Figure 21

D2: Apply gentle pressure (Figure 21)

- Apply gentle pressure to the injection site with a dry cotton ball or sterile gauze to prevent any bleeding.
- Do NOT rub or massage the injection site after administration.

Figure 22

D3: Check needle (Figure 22)

- Check through the green needle shield’s round windows that the needle was not damaged during administration.
- If any damage or malfunction to the needle is suspected please contact 1-866-604-3268

Figure 23

D4: Throw away / Disposal (Figure 23)

- DO NOT remove needle from syringe
- Dispose of complete product in sharps disposal container
- Do not dispose of the syringe or needle in the regular trash.
- The syringe and needle are not reusable.

3 DOSAGE FORMS AND STRENGTHS

Injection: 60 mg/0.2 mL, 90 mg/0.3 mL, and 120 mg/0.5 mL of lanreotide in single-dose, prefilled syringes packaged with a safety needle. The prefilled syringes contain a white to pale yellow, semi-solid formulation.

4 CONTRAINDICATIONS

Lanreotide Injection is contraindicated in patients with history of a hypersensitivity to lanreotide. Allergic reactions (including angioedema and anaphylaxis) have been reported following administration of lanreotide [see Adverse Reactions (6.3)].

5 WARNINGS AND PRECAUTIONS

5.1 Cholelithiasis and Complications of Cholelithiasis

Lanreotide Injection may reduce gallbladder motility and lead to gallstone formation; therefore, patients may need to be monitored periodically [see Adverse Reactions (6.1), Clinical Pharmacology (12.2)]. There have been postmarketing reports of cholelithiasis (gallstones) resulting in complications, including cholecystitis, cholangitis, and pancreatitis, and requiring cholecystectomy in patients taking lanreotide. If complications of cholelithiasis are suspected, discontinue Lanreotide Injection and treat appropriately.

5.2 Hyperglycemia and Hypoglycemia

Pharmacological studies in animals and humans show that lanreotide, like somatostatin and other somatostatin analogs, inhibits the secretion of insulin and glucagon. Hence, patients treated with Lanreotide Injection may experience hypoglycemia or hyperglycemia. Blood glucose levels should be monitored when Lanreotide Injection treatment is initiated, or when the dose is altered, and antidiabetic treatment should be adjusted accordingly [see Adverse Reactions (6.1)].

5.3 Cardiovascular Abnormalities

The most common overall cardiac adverse reactions observed in three pooled lanreotide injection cardiac studies in patients with acromegaly were sinus bradycardia (12/217, 5.5%), bradycardia (6/217, 2.8%), and hypertension (12/217, 5.5%) [see Adverse Reactions (6.1)].

In 81 patients with baseline heart rates of 60 beats per minute (bpm) or greater treated with lanreotide in Study 3, the incidence of heart rate less than 60 bpm was 23% (19/81) as compared to 16% (15/94) of placebo treated patients; 10 patients (12%) had documented heart rates less than 60 bpm on more than one visit. The incidence of documented episodes of heart rate less than 50 bpm as well as the incidence of bradycardia reported as an adverse event was 1% in each treatment group. Initiate appropriate medical management in patients who develop symptomatic bradycardia.

In patients without underlying cardiac disease, Lanreotide Injection may lead to a decrease in heart rate without necessarily reaching the threshold of bradycardia. In patients suffering from cardiac disorders prior to Lanreotide Injection treatment, sinus bradycardia may occur. Care should be taken when initiating treatment with Lanreotide Injection in patients with bradycardia.

5.4 Thyroid Function Abnormalities

Slight decreases in thyroid function have been seen during treatment with lanreotide in acromegalic patients, though clinical hypothyroidism is rare (less than 1%). Thyroid function tests are recommended where clinically indicated.

5.5 Monitoring: Laboratory Tests

Acromegaly: Serum GH and IGF-1 levels are useful markers of the disease and the effectiveness of treatment [see Dosage and Administration (2.1)].

5.6 Steatorrhea and Malabsorption of Dietary Fats

New onset steatorrhea, stool discoloration and loose stools have been reported in patients receiving somatostatin analogs, including lanreotide products. Somatostatin analogs reversibly inhibit secretion of pancreatic enzymes and bile acids, which may result in malabsorption of dietary fats and subsequent symptoms of steatorrhea, loose stools, abdominal bloating, and weight loss. If new occurrence or worsening of these symptoms are reported in patients receiving Lanreotide Injection, evaluate patients for potential pancreatic exocrine insufficiency and manage accordingly.

6 ADVERSE REACTIONS

The following adverse reactions are discussed in greater detail in other sections of the labeling:

- Cholelithiasis and Complications of Cholelithiasis [see Warnings and Precautions (5.1)]
- Hyperglycemia and Hypoglycemia [see Warnings and Precautions (5.2)]
- Cardiovascular Abnormalities [see Warnings and Precautions (5.3)]
- Thyroid Function Abnormalities [see Warnings and Precautions (5.4)]
- Steatorrhea and Malabsorption of Dietary Fats [see Warnings and Precautions (5.6)]

6.1 Clinical Trials Experience

Because clinical trials are conducted under widely varying conditions, adverse reaction rates observed in the clinical trials of a drug cannot be directly compared to rates in the clinical trials of another drug and may not reflect the rates observed in practice.

The safety of Lanreotide Injection was established from adequate and well-controlled studies of another lanreotide injection product [see Clinical Studies (14)]. Adverse reactions observed in these adequate and well-controlled studies are described below.

Acromegaly

The data described below reflect exposure to lanreotide injection in 416 acromegalic patients in seven studies. One study was a fixed-dose pharmacokinetic study. The other six studies were open-label or extension studies, one had a placebo-controlled, run-in period, and another had an active control. The population was mainly White (329/353, 93%) with a median age of 53 years of age (range 19 to 84 years). Fifty-four subjects (13%) were age 66 to 74 and 18 subjects (4.3%) were 75 years of age and older.

Patients were evenly matched for sex (205 males and 211 females). The median average monthly dose was 91.2 mg (e.g., 90 mg injected via the deep subcutaneous route every 4 weeks) over 385 days with a median cumulative dose of 1290 mg. Of the patients reporting acromegaly, severity at baseline (N=265), serum GH levels were less than 10 ng/mL for 69% (183/265) of the patients and 10 ng/mL or greater for 31% (82/265) of the patients.

The most commonly reported adverse reactions reported by greater than 5% of patients who received lanreotide (N=416) in the overall pooled safety studies in acromegaly patients were gastrointestinal disorders (diarrhea, abdominal pain, nausea, constipation, flatulence, vomiting, loose stools), cholelithiasis, and injection site reactions.

Tables 1 and 2 present adverse reaction data from clinical studies with lanreotide in acromegalic patients. The tables include data from a single clinical study and pooled data from seven clinical studies.

Adverse Reactions in Parallel Fixed-Dose Phase of Study 1

The incidence of treatment-emergent adverse reactions for lanreotide injection 60, 90, and 120 mg by dose as reported during the first 4 months (fixed-dose phase) of Study 1 [see Clinical Studies (14.1)] are provided in Table 1.

Table 1: Adverse Reactions in Patients with Acromegaly at an Incidence of Greater than 5% with Lanreotide Overall and Occurring at Higher Rate than Placebo: Placebo-Controlled and Fixed-Dose Phase of Study 1 By Dose
 | Placebo-Controlled Double-Blind Phase Weeks 0 to 4 |  | Fixed-Dose Phase Double-Blind + Single-Blind Weeks 0 to 20
Body System Preferred Term | Placebo (N=25) | Lanreotide Overall (N=83) | Lanreotide 60 mg (N=34) | Lanreotide 90 mg (N=36) | Lanreotide 120 mg (N=37) | Lanreotide Overall (N=107)
 | N (%) | N (%) | N (%) | N (%) | N (%) | N (%)
Gastrointestinal System Disorders | 1 (4%) | 30 (36%) | 12 (35%) | 21 (58%) | 27 (73%) | 60 (56%)
Diarrhea Abdominal pain Flatulence | 0 1 (4%) 0 | 26 (31%) 6 (7%) 5 (6%) | 9 (26%) 3 (9%) 0 (0%) | 15 (42%) 6 (17%) 3 (8%) | 24 (65%) 7 (19%) 5 (14%) | 48 (45%) 16 (15%) 8 (7%)
Application Site Disorders (Injection site mass/ pain/ reaction/ inflammation) | 0 (0%) | 5 (6%) | 3 (9%) | 4 (11%) | 8 (22%) | 15 (14%)
Liver and Biliary System Disorders | 1 (4%) | 3 (4%) | 9 (26%) | 7 (19%) | 4 (11%) | 20 (19%)
Cholelithiasis | 0 | 2 (2%) | 5 (15%) | 6 (17%) | 3 (8%) | 14 (13%)
Heart Rate & Rhythm Disorders | 0 | 8 (10%) | 7 (21%) | 2 (6%) | 5 (14%) | 14 (13%)
Bradycardia | 0 | 7 (8%) | 6 (18%) | 2 (6%) | 2 (5%) | 10 (9%)
Red Blood Cell Disorders | 0 | 6 (7%) | 2 (6%) | 5 (14%) | 2 (5%) | 9 (8%)
Anemia | 0 | 6 (7%) | 2 (6%) | 5 (14%) | 2 (5%) | 9 (8%)
Metabolic & Nutritional Disorders | 3 (12%) | 13 (16%) | 8 (24%) | 9 (25%) | 4 (11%) | 21 (20%)
Weight decrease | 0 | 7 (8%) | 3 (9%) | 4 (11%) | 2 (5%) | 9 (8%)
A patient is counted only once for each body system and preferred term.
Dictionary = WHOART.

In Study 1, the adverse reactions of diarrhea, abdominal pain, and flatulence increased in incidence with increasing dose of lanreotide injection .

Adverse Reactions in Long-Term Clinical Trials

Table 2 provides the most common adverse reactions (greater than 5%) that occurred in 416 acromegalic patients treated with lanreotide injection pooled from 7 studies compared to those patients from the 2 efficacy studies (Studies 1 and 2). Patients with elevated GH and IGF-1 levels were either naive to somatostatin analog therapy or had undergone a 3-month washout [see Clinical Studies (14.1)].

Table 2: Adverse Reactions in Lanreotide -Treated Patients with Acromegaly at an Incidence Greater than 5% in Overall Group Versus Adverse Reactions Reported in Studies 1 and 2
System Organ Class | Number and Percentage of Patients
System Organ Class | Studies 1 & 2 (N=170) |  | Overall Pooled Data (N=416)
System Organ Class | N | % | N | %
Patients with any Adverse Reactions | 157 | 92 | 356 | 86
Gastrointestinal disorders | 121 | 71 | 235 | 57
Diarrhea | 81 | 48 | 155 | 37
Abdominal pain | 34 | 20 | 79 | 19
Nausea | 15 | 9 | 46 | 11
Constipation | 9 | 5 | 33 | 8
Flatulence | 12 | 7 | 30 | 7
Vomiting | 8 | 5 | 28 | 7
Loose stools | 16 | 9 | 23 | 6
Hepatobiliary disorders | 53 | 31 | 99 | 24
Cholelithiasis | 45 | 27 | 85 | 20
General disorders and administration site conditions | 51 | 30 | 91 | 22
(Injection site pain /mass /induration/ nodule/pruritus) | 28 | 17 | 37 | 9
Musculoskeletal and connective tissue disorders | 44 | 26 | 70 | 17
Arthralgia | 17 | 10 | 30 | 7
Nervous system disorders | 34 | 20 | 80 | 19
Headache | 9 | 5 | 30 | 7
Dictionary = MedDRA 7.1

In addition to the adverse reactions listed in Table 2, the following reactions were also seen:

- Sinus bradycardia occurred in 7% (12) of patients in the pooled Study 1 and 2 and in 3% (13) of patients in the overall pooled studies.
- Hypertension occurred in 7% (11) of patients in the pooled Study 1 and 2 and in 5% (20) of patients in the overall pooled studies.

- Anemia occurred in 7% (12) of patients in the pooled Study 1 and 2 and in 3% (14) of patients in the overall pooled studies.

Gastrointestinal Adverse Reactions

In the pooled clinical studies of lanreotide therapy, a variety of gastrointestinal (GI) reactions occurred, the majority of which were mild to moderate in severity. One percent of acromegalic patients treated with lanreotide in the pooled clinical studies discontinued treatment because of gastrointestinal reactions.

Pancreatitis was reported in less than 1% of patients.

Gallbladder Adverse Reactions

In clinical studies involving 416 acromegalic patients treated with lanreotide, cholelithiasis and gallbladder sludge were reported in 20% of the patients. Among 167 acromegalic patients treated with lanreotide who underwent routine evaluation with gallbladder ultrasound, 17% had gallstones at baseline. New cholelithiasis was reported in 12% of patients. Cholelithiasis may be related to dose or duration of exposure [see Warnings and Precautions (5.1)].

Injection Site Reactions

In the pooled clinical studies, injection site pain (4%) and injection site mass (2%) were the most frequently reported local adverse drug reactions that occurred with the administration of lanreotide. In a specific analysis, 20 of 413 patients (5%) presented indurations at the injection site. Injection site adverse reactions were more commonly reported soon after the start of treatment and were less commonly reported as treatment continued. Such adverse reactions were usually mild or moderate but did lead to withdrawal from clinical studies in two subjects.

Glucose Metabolism Adverse Reactions

In the clinical studies in acromegalic patients treated with lanreotide, adverse reactions of dysglycemia (hypoglycemia, hyperglycemia, diabetes) were reported by 14% (47/332) of patients and were considered related to study drug in 7% (24/332) of patients [see Warnings and Precautions (5.2)].

Cardiac Adverse Reactions

In the pooled clinical studies, sinus bradycardia (3%) was the most frequently observed heart rate and rhythm disorder. All other cardiac adverse drug reactions were observed in less than 1% of patients. The relationship of these events to lanreotide could not be established because many of these patients had underlying cardiac disease [see Warnings and Precautions (5.3)].

A comparative echocardiography study of lanreotide and another somatostatin analog demonstrated no difference in the development of new or worsening valvular regurgitation between the 2 treatments over 1 year. The occurrence of clinically significant mitral regurgitation (i.e., moderate or severe in intensity) or of clinically significant aortic regurgitation (i.e., at least mild in intensity) was low in both groups of patients throughout the study.

Other Adverse Reactions

For the most commonly occurring adverse reactions in the pooled analysis, diarrhea, abdominal pain, and cholelithiasis, there was no apparent trend for increasing incidence with age. GI disorders and renal and urinary disorders were more common in patients with documented hepatic impairment; however, the incidence of cholelithiasis was similar between groups.

Gastroenteropancreatic Neuroendocrine Tumors

The safety of lanreotide injection 120 mg for the treatment of patients with gastroenteropancreatic neuroendocrine tumors (GEP-NETs) was evaluated in Study 3, a double-blind, placebo-controlled trial. Patients in Study 3 were randomized to receive lanreotide (N=101) or placebo (N=103) administered by deep subcutaneous injection once every 4 weeks. The data below reflect exposure to lanreotide in 101 patients with GEP-NETs, including 87 patients exposed for at least 6 months and 72 patients exposed for at least 1 year (median duration of exposure 22 months). Patients treated with lanreotide had a median age of 64 years (range 30 to 83 years), 53% were men and 96% were White. Eighty-one percent of patients (83/101) in the lanreotide arm and 82% of patients (82/103) in the placebo arm did not have disease progression within 6 months of enrollment and had not received prior therapy for GEP-NETs. The rates of discontinuation due to treatment-emergent adverse reactions were 5% (5/101 patients) in the lanreotide arm and 3% (3/103 patients) in the placebo arm.

Table 3 compares the adverse reactions reported with an incidence of 5% and greater in patients receiving lanreotide injection 120 mg administered every 4 weeks and reported more commonly than placebo.

Table 3: Adverse Reactions Occurring in 5% and Greater of Lanreotide -Treated Patients with GEP-NETs and at a Higher Rate Than in Placebo -Treated Patients in Study 3
Adverse Reaction | Lanreotide 120 mg N=101 |  | Placebo N=103
Adverse Reaction | Any (%) | Severe** (%) | Any (%) | Severe** (%)
Any Adverse Reactions | 88 | 26 | 90 | 31
Abdominal pain^1 | 34* | 6* | 24* | 4
Musculoskeletal pain^2 | 19* | 2* | 13* | 2
Vomiting | 19* | 2* | 9* | 2*
Headache | 16 | 0 | 11 | 1
Injection site reaction^3 | 15 | 0 | 7 | 0
Hyperglycemia^4 | 14* | 0 | 5 | 0
Hypertension^5 | 14* | 1* | 5 | 0
Cholelithiasis | 14* | 1* | 7 | 0
Dizziness | 9 | 0 | 2* | 0
Depression^6 | 7 | 0 | 1 | 0
Dyspnea | 6 | 0 | 1 | 0
^1Includes preferred terms of abdominal pain, abdominal pain upper/lower, abdominal discomfort
^2 Includes preferred terms of myalgia, musculoskeletal discomfort, musculoskeletal pain, back pain
^3 Includes preferred terms of infusion site extravasation, injection site discomfort, injection site granuloma, injections site hematoma, injection site hemorrhage, injection site induration, injection site mass, injections site nodule, injection site pain, injection site pruritus, injection site rash, injection site reaction, injection site swelling
^4 Includes preferred terms of diabetes mellitus, glucose tolerance impaired, hyperglycemia, type 2 diabetes mellitus
^5 Includes preferred terms of hypertension, hypertensive crisis
^6 Includes preferred terms of depression, depressed mood
* Includes one or more serious adverse events (SAEs) defined as any event that results in death, is life threatening, results in hospitalization or prolongation of hospitalization, results in persistent or significant disability, results in congenital anomaly/birth defect, or may jeopardize the patient and may require medical or surgical intervention to prevent one of the outcomes listed.
** Defined as hazardous to well-being, significant impairment of function or incapacitation

Carcinoid Syndrome

The safety of lanreotide injection 120 mg in patients with histopathologically confirmed neuroendocrine tumors and a history of carcinoid syndrome (flushing and/or diarrhea) was evaluated in Study 4, a double-blind, placebo-controlled trial. Patients were randomized to receive lanreotide injection (N=59) or placebo (N=56) administered by deep subcutaneous injection once every 4 weeks. Patients in both arms of Study 4 had access to subcutaneous octreotide as rescue medication for symptom control.

Adverse reactions reported in Study 4 were generally similar to those reported in Study 3 for the GEP-NETs population shown in Table 3 above. Adverse reactions occurring in Study 4 in 5% and greater of lanreotide-treated patients and occurring at least 5% more than in placebo-treated patients were headache (12% vs 5%, respectively), dizziness (7% vs 0%, respectively), and muscle spasm (5% vs 0%, respectively) by week 16.

6.2 Postmarketing Experience

The following adverse reactions have been identified during post-approval use of lanreotide. Because these reactions are reported voluntarily from a population of uncertain size, it is not always possible to reliably estimate their frequency or establish a causal relationship to drug exposure.

Gastrointestinal disorders: pancreatic exocrine insufficiency

Hepatobiliary: steatorrhea; cholecystitis, cholangitis, pancreatitis, which have sometimes required cholecystectomy

Hypersensitivity: angioedema and anaphylaxis

Injection site reactions: injection site abscess

7 DRUG INTERACTIONS

7.1 Insulin and Oral Hypoglycemic Drugs

Lanreotide, like somatostatin and other somatostatin analogs, inhibits the secretion of insulin and glucagon. Therefore, blood glucose levels should be monitored when Lanreotide Injection treatment is initiated or when the dose is altered, and antidiabetic treatment should be adjusted accordingly [see Warnings and Precautions (5.2)].

7.2 Cyclosporine

Concomitant administration of cyclosporine with Lanreotide Injection may decrease the absorption of cyclosporine, and therefore, may necessitate adjustment of cyclosporine dose to maintain therapeutic drug concentrations. [see Clinical Pharmacology (12.3)]

7.3 Bromocriptine

Limited published data indicate that concomitant administration of a somatostatin analog and bromocriptine may increase the absorption of bromocriptine [see Clinical Pharmacology (12.3)].

7.4 Bradycardia-Inducing Drugs

Concomitant administration of bradycardia-inducing drugs (e.g., beta-blockers) may have an additive effect on the reduction of heart rate associated with lanreotide. Dosage adjustments of concomitant drugs may be necessary.

7.5 Drug Metabolism Interactions

The limited published data available indicate that somatostatin analogs may decrease the metabolic clearance of compounds known to be metabolized by cytochrome P450 enzymes, which may be due to the suppression of growth hormone. Since it cannot be excluded that Lanreotide Injection may have this effect, avoid other drugs mainly metabolized by CYP3A4 and which have a low therapeutic index (e.g., quinidine, terfenadine). Drugs metabolized by the liver may be metabolized more slowly during Lanreotide Injection treatment and dose reductions of the concomitantly administered medications should be considered [see Clinical Pharmacology (12.3)].

8 USE IN SPECIFIC POPULATIONS

8.1 Pregnancy

Risk Summary

Limited available data based on post-marketing case reports with lanreotide use in pregnant women are not sufficient to determine a drug-associated risk of adverse developmental outcomes. In animal reproduction studies, decreased embryo/fetal survival was observed in pregnant rats and rabbits at subcutaneous doses 5- and 2-times the maximum recommended human dose (MRHD) of 120 mg, respectively (see Data)

The background risk of major birth defects and miscarriage for the indicated populations is unknown. All pregnancies have a background risk of birth defect, loss, or other adverse outcomes. In the U.S. general population, the estimated background risk of major birth defects and miscarriage in clinically recognized pregnancies is 2% to 4% and 15% to 20%, respectively.

Data

Animal Data

A reproductive study in pregnant rats given 30 mg/kg of lanreotide by subcutaneous injection every 2 weeks (5 times the human dose, based on body surface area comparisons) resulted in decreased embryo/fetal survival. A study in pregnant rabbits given subcutaneous injections of 0.45 mg/kg/day (2 times the human therapeutic exposures at the maximum recommended dose of 120 mg, based on comparisons of relative body surface area) shows decreased fetal survival and increased fetal skeletal/soft tissue abnormalities.

8.2 Lactation

Risk Summary

There is no information available on the presence of lanreotide in human milk, the effects of the drug on the breastfed infant, or the effects of the drug on milk production. Studies show that lanreotide administered subcutaneously passes into the milk of lactating rats; however, due to specifies-specific differences in lactation physiology, animal data may not reliably predict drug levels in human milk. Because of the potential for serious adverse reactions in breastfed infants from Lanreotide Injection, including effects on glucose metabolism and bradycardia, advise women not to breastfeed during treatment with Lanreotide Injection and for 6 months (6 half-lives) following the last dose.

8.3 Females and Males of Reproductive Potential

Infertility

Females

Based on results from animal studies conducted in female rats, Lanreotide Injection may reduce fertility in females of reproductive potential [see Nonclinical Toxicology (13.1)].

8.4 Pediatric Use

The safety and effectiveness of Lanreotide Injection in pediatric patients have not been established.

8.5 Geriatric Use

No overall differences in safety or effectiveness were observed between elderly patients with acromegaly compared with younger patients and other reported clinical experience has not identified differences in responses between the elderly and younger patients, but greater sensitivity of some older individuals cannot be ruled out. Studies 3 and 4, conducted in patients with neuroendocrine tumors, did not include sufficient numbers of patients aged 65 and over to determine whether they respond differently from younger patients.

Other reported clinical experience has not identified differences in responses between the elderly and younger patients. In general, dose selection for an elderly patient should be cautious, usually starting at the low end of the dosing range, reflecting the greater frequency of decreased hepatic, renal, or cardiac function, and of concomitant disease or other drug therapy.

8.6 Renal Impairment

Acromegaly

Lanreotide has been studied in patients with end-stage renal function on dialysis, but has not been studied in patients with mild, moderate, or severe renal impairment. It is recommended that patients with moderate or severe renal impairment receive a starting dose of Lanreotide Injection of 60 mg. Caution should be exercised when considering patients with moderate or severe renal impairment for an extended dosing interval of Lanreotide Injection 120 mg every 6 or 8 weeks [see Dosage and Administration (2.4) and Clinical Pharmacology (12.3)].

Neuroendocrine Tumors (NET) – Gastroenteropancreatic Neuroendocrine Tumors

No effect was observed in total clearance of lanreotide in patients with mild to moderate renal impairment receiving lanreotide injection 120 mg. Patients with severe renal impairment were not studied [see Clinical Pharmacology (12.3)].

8.7 Hepatic Impairment

Acromegaly

It is recommended that patients with moderate or severe hepatic impairment receive a starting dose of Lanreotide Injection 60 mg. Caution should be exercised when considering patients with moderate or severe hepatic impairment for an extended dosing interval of Lanreotide Injection 120 mg every 6 or 8 weeks [see Dosage and Administration (2.4) and Clinical Pharmacology (12.3)].

Neuroendocrine Tumors (NET) – Gastroenteropancreatic Neuroendocrine Tumors

Lanreotide has not been studied in patients with hepatic impairment.

11 DESCRIPTION

Lanreotide Injection 60 mg/0.2 mL, 90 mg/0.3 mL, and 120 mg/0.5 mL is a prolonged-release formulation for deep subcutaneous injection. It contains the drug substance lanreotide acetate, a synthetic octapeptide with a biological activity similar to naturally occurring somatostatin, water for injection and acetic acid (for pH adjustment).

Lanreotide Injection is available as sterile, ready-to-use, single-dose prefilled syringes containing lanreotide acetate supersaturated bulk solution of 24.6% w/w lanreotide base.

Each syringe contains: | Lanreotide Injection 60 mg/0.2 mL | Lanreotide Injection 90 mg/0.3 mL | Lanreotide Injection 120 mg/0.5 mL
Lanreotide acetate | 89.9 mg | 123.2 mg | 156.6 mg
Acetic Acid | q.s. | q.s. | q.s.
Water for injection | 236.4 mg | 324.1 mg | 411.6 mg
Total Weight | 328.9 mg | 450.9 mg | 572.8 mg

Lanreotide acetate is a synthetic cyclical octapeptide analog of the natural hormone, somatostatin. Lanreotide acetate is chemically known as [cyclo S-S]-3-(2-naphthyl)-D alanyl-L-cysteinyl-L-tyrosyl-D-tryptophyl-L-lysyl-L-valyl-L-cysteinyl-L-threoninamide, acetate salt. Its molecular weight is 1096.34 (base) and its amino acid sequence is:

The Lanreotide Injection in the prefilled syringe is a white to pale yellow, semi-solid formulation.

12 CLINICAL PHARMACOLOGY

12.1 Mechanism of Action

Lanreotide, the active component of Lanreotide Injection, is an octapeptide analog of natural somatostatin. The mechanism of action of lanreotide is believed to be similar to that of natural somatostatin.

12.2 Pharmacodynamics

Lanreotide has a high affinity for human somatostatin receptors (SSTR) 2 and 5 and a reduced binding affinity for human SSTR1, 3, and 4. Activity at human SSTR2 and 5 is the primary mechanism believed responsible for GH inhibition. Like somatostatin, lanreotide is an inhibitor of various endocrine, neuroendocrine, exocrine, and paracrine functions.

The primary pharmacodynamic effect of lanreotide is a reduction of GH and/or IGF-1 levels enabling normalization of levels in acromegalic patients [see Clinical Studies (14.1)]. In acromegalic patients, lanreotide reduces GH levels in a dose-dependent way. After a single injection of lanreotide, plasma GH levels fall rapidly and are maintained for at least 28 days.

In Study 4, patients with carcinoid syndrome treated with lanreotide injection 120 mg every 4 weeks had reduced levels of urinary 5-hydroxyindoleacetic acid (5-HIAA) compared with placebo [see Clinical Studies (14.3)].

Lanreotide inhibits the basal secretion of motilin, gastric inhibitory peptide, and pancreatic polypeptide, but has no significant effect on the secretion of secretin. Lanreotide inhibits postprandial secretion of pancreatic polypeptide, gastrin, and cholecystokinin (CCK). In healthy subjects, lanreotide produces a reduction and a delay in postprandial insulin secretion, resulting in transient, mild glucose intolerance.

Lanreotide inhibits meal-stimulated pancreatic secretions, and reduces duodenal bicarbonate and amylase concentrations, and produces a transient reduction in gastric acidity.

Lanreotide has been shown to inhibit gallbladder contractility and bile secretion in healthy subjects [see Warnings and Precautions (5.1)].

In healthy subjects, lanreotide inhibits meal-induced increases in superior mesenteric artery and portal venous blood flow but has no effect on basal or meal-stimulated renal blood flow. Lanreotide has no effect on renal plasma flow or renal vascular resistance. However, a transient decrease in glomerular filtration rate (GFR) and filtration fraction has been observed after a single injection of lanreotide.

In healthy subjects, non-significant reductions in glucagon levels were seen after lanreotide administration. In diabetic non-acromegalic subjects receiving a continuous infusion (21-day) of lanreotide, serum glucose concentrations were temporarily decreased by 20% to 30% after the start and end of the infusion. Serum glucose concentrations returned to normal levels within 24 hours. A significant decrease in insulin concentrations was recorded between baseline and Day 1 only [see Warnings and Precautions (5.2)].

Lanreotide inhibits the nocturnal increase in thyroid-stimulating hormone (TSH) seen in healthy subjects. Lanreotide reduces prolactin levels in acromegalic patients treated on a long-term basis [see Warnings and Precautions (5.4)].

12.3 Pharmacokinetics

Lanreotide Injection is thought to form a drug depot at the injection site due to the interaction of the formulation with physiological fluids. The most likely mechanism of drug release is a passive diffusion of the precipitated drug from the depot towards the surrounding tissues, followed by the absorption to the bloodstream.

After a single, deep subcutaneous administration, the mean absolute bioavailability of lanreotide in healthy subjects was 73.4, 69.0, and 78.4% for the 60 mg, 90 mg, and 120 mg doses, respectively. Mean Cmax values ranged from 4.3 to 8.4 ng/mL during the first day. Single-dose linearity was demonstrated with respect to AUC and Cmax and showed high inter-subject variability. Lanreotide showed sustained release of lanreotide with a half-life of 23 to 30 days. Mean serum concentrations were > 1 ng/mL throughout 28 days at 90 mg and 120 mg and > 0.9 ng/mL at 60 mg.

In studies evaluating excretion, <5% of lanreotide was excreted in urine and less than 0.5% was recovered unchanged in feces, indicative of some biliary excretion.

Acromegaly

In a repeat-dose administration pharmacokinetics (PK) study in acromegalic patients, rapid initial release was seen giving peak levels during the first day after administration. At doses of lanreotide between 60 and 120 mg, linear pharmacokinetics were observed in acromegalic patients. At steady state, mean Cmax values were 3.8 ± 0.5, 5.7 ± 1.7, and 7.7 ± 2.5 ng/mL, increasing linearly with dose. The mean accumulation ratio index was 2.7, which is in line with the range of values for the half-life of lanreotide. The steady- state trough serum lanreotide concentrations in patients receiving lanreotide every 28 days were 1.8 ± 0.3; 2.5 ± 0.9 and 3.8 ± 1.0 ng/mL at 60 mg, 90 mg, and 120 mg doses, respectively. A limited initial burst effect and a low peak-to-trough fluctuation (81% to 108%) of the serum concentration at the plateau were observed.

For the same doses, similar values were obtained in clinical studies after at least four administrations (2.3 ± 0.9, 3.2 ± 1.1, and 4.0 ± 1.4 ng/mL, respectively).

Pharmacokinetic data from studies evaluating extended dosing use of lanreotide injection 120 mg demonstrated mean steady-state, Cmin values between 1.6 and 2.3 ng/mL for the 8- and 6-week treatment interval, respectively.

Gastroenteropancreatic Neuroendocrine Tumors

In patients with GEP-NETs treated with lanreotide 120 mg every 4 weeks, steady state concentrations were reached after 4 to 5 injections and the mean trough serum lanreotide concentrations at steady state ranged from 5.3 to 8.6 ng/mL.

Specific Populations

Lanreotide Injection has not been studied in specific populations. However, the pharmacokinetics of lanreotide in renal impaired, hepatic impaired, and geriatric subjects were evaluated after IV administration of lanreotide immediate release formulation (IRF) at 7 mcg/kg dose.

Geriatric Patients

Studies in healthy elderly subjects showed an 85% increase in half-life and a 65% increase in mean residence time (MRT) of lanreotide compared to those seen in healthy young subjects; however, there was no change in either AUC or Cmax of lanreotide in elderly as compared to healthy young subjects. Age has no effect on clearance of lanreotide based on population PK analysis in patients with GEP-NET which included 122 patients aged 65 to 85 years with neuroendocrine tumors.

Patients with Renal Impairment

An approximate 2-fold decrease in total serum clearance of lanreotide, with a consequent 2fold increase in half-life and AUC was observed [see Dosage and Administration (2.2) and Use in Specific Populations (8.6)].

Mild (CLcr 60-89 mL/min) or moderate (CLcr 30-59 mL/min) renal impairment has no effect on clearance of lanreotide in patients with GEP-NET based on population PK analysis which included 106 patients with mild and 59 patients with moderate renal impairment treated with lanreotide. GEP-NET patients with severe renal impairment (CLcr < 30 mL/min) were not studied.

Patients with Hepatic Impairment

In subjects with moderate to severe hepatic impairment, a 30% reduction in clearance of lanreotide was observed [see Dosage and Administration (2.3) and Use in Specific Populations (8.7)].

The effect of hepatic impairment on clearance of lanreotide has not been studied in patients with GEP-NET.

12.6 Immunogenicity

The observed incidence of anti-drug antibodies is highly dependent on the sensitivity and specificity of the assay. Differences in assay methods preclude meaningful comparisons of the incidence of anti-drug antibodies in the studies described below with the incidence of anti-drug antibodies in other studies, including those of Lanreotide Injection or of other lanreotide products.

Acromegaly

Laboratory investigations of acromegalic patients treated with lanreotide injection in clinical studies show that the percentage of patients with putative antibodies at any time point after treatment is low (less than 1% to 4% of patients in specific studies whose antibodies were tested). The antibodies did not appear to affect the efficacy or safety of lanreotide injection.

GEP-NETs

In Study 3, development of anti-lanreotide antibodies was assessed using a radioimmunoprecipitation assay. In patients with GEP-NETs receiving lanreotide injection, the incidence of anti-lanreotide antibodies was 4% (3 of 82) at 24 weeks, 10% (7 of 67) at 48 weeks, 11% (6 of 57) at 72 weeks, and 10% (8 of 84) at 96 weeks. Assessment for neutralizing antibodies was not conducted.

Carcinoid Syndrome

In Study 4, less than 2% (2 of 108) of the patients treated with lanreotide injection developed anti-lanreotide antibodies.

13 NONCLINICAL TOXICOLOGY

13.1 Carcinogenesis, Mutagenesis, Impairment of Fertility

Standard lifetime carcinogenicity bioassays were conducted in mice and rats. Mice were given daily subcutaneous doses of lanreotide at 0.5, 1.5, 5, 10, and 30 mg/kg for 104 weeks. Cutaneous and subcutaneous tumors of fibrous connective tissues at the injection sites were observed at the high dose of 30 mg/kg/day. Fibrosarcomas in both genders and malignant fibrous histiocytomas were observed in males at 30 mg/kg/day resulting in exposures 3 times higher than the clinical therapeutic exposure at the maximum therapeutic dose of 120 mg given by monthly subcutaneous injection based on the AUC values. Rats were given daily subcutaneous doses of lanreotide at 0.1, 0.2, and 0.5 mg/kg for 104 weeks. Increased cutaneous and subcutaneous tumors of fibrous connective tissues at the injection sites were observed at the dose of 0.5 mg/kg/day resulting in exposures less than the clinical therapeutic exposure at 120 mg given by monthly subcutaneous injection. The increased incidence of injection site tumors in rodents is likely related to the increased dosing frequency (daily) in animals compared to monthly dosing in humans and therefore may not be clinically relevant.

Lanreotide was not genotoxic in tests for gene mutations in a bacterial mutagenicity (Ames) assay, or mouse lymphoma cell assay with or without metabolic activation. Lanreotide was not genotoxic in tests for the detection of chromosomal aberrations in a human lymphocyte and in vivo mouse micronucleus assay.

In a fertility study conducted with lanreotide in rats, reduced female fecundity was observed at estimated exposure corresponding to approximately 10-fold the plasma exposure at the MRHD of 120 mg. The fertility of male rats was unaffected by the treatment up to an estimated exposure corresponding to approximately 11-fold the plasma exposure at the MRHD of 120 mg.

14 CLINICAL STUDIES

The safety and efficacy of Lanreotide Injection have been established based on adequate and well-controlled studies of another lanreotide injection product. Below is a description of the results of these adequate and well-controlled studies of lanreotide injection in these conditions.

14.1 Acromegaly

The effect of lanreotide on reducing GH and IGF-levels and control of symptoms in patients with acromegaly was studied in 2 long-term, multiple-dose, randomized, multicenter studies.

Study 1

This 1-year study included a 4-week, double-blind, placebo-controlled phase; a 16-week single-blind, fixed-dose phase; and a 32-week, open-label, dose-titration phase. Patients with active acromegaly, based on biochemical tests and medical history, entered a 12-week washout period if there was previous treatment with a somatostatin analog or a dopaminergic agonist.

Upon entry, patients were randomly allocated to receive a single, deep subcutaneous injection of lanreotide 60, 90, or 120 mg or placebo. Four weeks later, patients entered a fixed-dose phase where they received 4 injections of lanreotide followed by a dose-titration phase of 8 injections for a total of 13 injections over 52 weeks (including the placebo phase). Injections were given at 4-week intervals. During the dose-titration phase of the study, the dose was titrated twice (every fourth injection), as needed, according to individual GH and IGF-1 levels.

A total of 108 patients (51 males, 57 females) were enrolled in the initial placebo-controlled phase of the study. Half (54/108) of the patients had never been treated with a somatostatin analog or dopamine agonist or had stopped treatment for at least 3 months prior to their participation in the study, and were required to have a mean GH level greater than 5 ng/mL at their first visit. The other half of the patients had received prior treatment with a somatostatin analog or a dopamine agonist before study entry and at study entry were required to have a mean GH concentration greater than 3 ng/mL and at least a 100% increase in mean GH concentration after washout of medication.

One hundred and seven (107) patients completed the placebo-controlled phase, 105 patients completed the fixed-dose phase, and 99 patients completed the dose-titration phase. Patients not completing withdrew due to adverse events (5) or lack of efficacy (4).

In the double-blind phase of Study 1, a total of 52 (63%) of the 83 lanreotide-treated patients had a greater than 50% decrease in mean GH from baseline to Week 4, including 52%, 44%, and 90% of patients in the 60, 90, and 120 mg groups, respectively, compared to placebo (0%, 0/25). In the fixed-dose phase at Week 16, 72% of all 107 lanreotide-treated patients had a decrease from baseline in mean GH of greater than 50%, including 68% (23/34), 64% (23/36), and 84% (31/37) of patients in the 60, 90, and 120 mg lanreotide treatment groups, respectively. Efficacy achieved in the first 16 weeks was maintained for the duration of the study (see Table 4).

Table 4: Overall Efficacy Results Based on GH and IGF-1 Levels by Treatment Phase in Patients with Acromegaly in Study 1
 |  | Baseline N=107 | Before Titration 1 (16 weeks) N=107 | Before Titration 2 (32 weeks) N=105 | Last Value Available* N=107
IGH
≤5.0 ng/mL | Number of Responders (%) | 20 (19%) | 72 (67%) | 76 (72%) | 74 (69%)
≤2.5 ng/mL | Number of Responders (%) | 0 (0%) | 52 (49%) | 59 (56%) | 55 (51%)
≤1.0 ng/mL | Number of Responders (%) | 0 (0%) | 15 (14%) | 18 (17%) | 17 (16%)
Median GH | ng/mL | 10.27 | 2.53 | 2.20 | 2.43
GH Reduction | Median % Reduction | - | 75.5 | 78.2 | 75.5
IGF-1
Normal^3 | Number of Responders (%) | 9 (8%) | 58 (54%) | 57 (54%) | 62 (58%)
Median IGF-1 | ng/mL | 775.0 | 332.0^1 | 316.5^2 | 326.0
IGF-1 Reduction | Median % Reduction | -- | 52.3^1 | 54.5^2 | 55.4
IGF-1 Normal^3 + GH ≤2.5 ng/mL | Number of Responders (%) | 0 (0%) | 41 (38%) | 46 (44%) | 44 (41%)
^1n=105, ^2n=102, ^3Age-adjusted
*Last Observation Carried Forward

Study 2

This was a 48-week, open-label, uncontrolled, multicenter study that enrolled patients who had an IGF-1 concentration 1.3 times or greater than the upper limit of the normal age- adjusted range. Patients receiving treatment with a somatostatin analog (other than lanreotide) or a dopaminergic agonist had to attain this IGF-1 concentration after a washout period of up to 3 months.

Patients were initially enrolled in a 4-month, fixed-dose phase where they received 4 deep subcutaneous injections of lanreotide 90 mg, at 4-week intervals. Patients then entered a dose-titration phase where the dose of lanreotide was adjusted based on GH and IGF-1 levels at the beginning of the dose-titration phase and, if necessary, again after another 4 injections. Patients titrated up to the maximum dose (120 mg) were not allowed to titrate down again.

A total of 63 patients (38 males, 25 females) entered the fixed-dose phase of the trial and 57 patients completed 48 weeks of treatment. Six patients withdrew due to adverse reactions (3), other reasons (2), or lack of efficacy (1).

After 48 weeks of treatment with lanreotide at 4-week intervals, 43% (27/63) of the acromegalic patients in this study achieved normal age-adjusted IGF-1 concentrations. Mean IGF-1 concentrations after treatment completion were 1.3 ± 0.7 times the upper limit of normal compared to 2.5 ± 1.1 times the upper limit of normal at baseline.

The reduction in IGF-1 concentrations over time correlated with a corresponding marked decrease in mean GH concentrations. The proportion of patients with mean GH concentrations less than 2.5 ng/mL increased significantly from 35% to 77% after the fixed- dose phase and 85% at the end of the study. At the end of treatment, 24/63 (38%) of patients had both normal IGF-1 concentrations and a GH concentration of less than or equal to 2.5 ng/mL (see Table 5) and 17/63 patients (27%) had both normal IGF-1 concentrations and a GH concentration of less than 1 ng/mL.

Table 5: Overall Efficacy Results Based on GH and IGF-1 Levels by Treatment Phase in Patients with Acromegaly in Study 2
 |  | Baseline N=63 | Before Titration 1 (12 wks) N=63 | Before Titration 2 (28 wks) N=59 | Last Value Available* N=63
IGF-1
Normal1 | Number of Responders (%) | 0 (0%) | 17 (27%) | 22 (37%) | 27 (43%)
Median IGF-1 | ng/mL | 689.0 | 382.0 | 334.0 | 317.0
IGF-1 Reduction | Median % Reduction | -- | 41.0 | 51.0 | 50.3
GH
≤5.0 ng/mL | Number of Responders (%) | 40 (64%) | 59 (94%) | 57 (97%) | 62 (98%)
≤2.5 ng/mL | Number of Responders (%) | 21 (33%) | 47 (75%) | 47 (80%) | 54 (86%)
≤1.0 ng/mL | Number of Responders (%) | 8 (13%) | 19 (30%) | 18 (31%) | 28 (44%)
Median GH | ng/Ml | 3.71 | 1.65 | 1.48 | 1.13
GH Reduction | Median % Reduction | -- | 63.2 | 66.7 | 78.6^2
IGF-1 normal^1 + GH ≤2.5 ng/mL | Number of Responders (%) | 0 (0%) | 14 (22%) | 20 (34%) | 24 (38%)
^1Age-adjusted, ^2N= 62,
* Last Observation Carried Forward

Examination of age and gender subgroups did not identify differences in response to lanreotide among these subgroups. The limited number of patients in the different racial subgroups did not raise any concerns regarding efficacy of lanreotide in these subgroups.

14.2 Gastroenteropancreatic Neuroendocrine Tumors

The efficacy of lanreotide was established in a multicenter, randomized, double-blind, placebo-controlled trial of 204 patients with unresectable, well or moderately differentiated, metastatic or locally advanced, GEP-NETs. Patients were required to have non-functioning tumors without hormone-related symptoms. Patients were randomized 1:1 to receive lanreotide injection 120 mg (n=101) or placebo (n=103) every 4 weeks until disease progression, unacceptable toxicity, or a maximum of 96 weeks of treatment. Randomization was stratified by the presence or absence of prior therapy and by the presence or absence of disease progression within 6 months of enrollment. The major efficacy outcome measure was progression-free survival (PFS), defined as time to disease progression as assessed by central independent radiological review using the Response Evaluation Criteria in Solid Tumors (RECIST 1.0) or death.

The median patient age was 63 years (range 30 to 92 years) and 95% were White. Disease progression was present in nine of 204 patients (4.4%) in the 6 months prior to enrollment and 29 patients (14%) received prior chemotherapy. Ninety-one patients (45%) had primary sites of disease in the pancreas, with the remainder originating in the midgut (35%), hindgut (7%), or unknown primary location (13%). The majority (69%) of the study population had grade 1 tumors. Baseline prognostic characteristics were similar between arms with one exception: there were 39% of patients in the lanreotide arm and 27% of patients in the placebo arm who had hepatic involvement by tumor of greater than 25%.

Patients in the lanreotide arm had a statistically significant improvement in PFS compared to patients receiving placebo (see Table 6 and Figure 1).

Table 6: Efficacy Results in Patients with GEP-NETs in Study 3
 | Lanreotide | Placebo
 | n=101 | n=103
Number of Events (%) | 32 (31.7%) | 60 (58.3%)
Median PFS (months)(95% CI) | NE^1 (NE, NE) | 16.6 (11.2, 22.1)
HR (95% CI) | 0.47 (0.30, 0.73)^2
Log-rank p-value | <0.001
^1NE = not reached at 22 months
^2Hazard Ratio is derived from a Cox stratified proportional hazards model

Figure 1: Kaplan-Meier Curves of Progression-Free Survival in Patients with GEP-NETs in Study 3

14.3 Carcinoid Syndrome

Study 4 was a multicenter, randomized, 16-week, double-blind, placebo-controlled trial in 115 patients with histopathologically-confirmed neuroendocrine tumors and a history of carcinoid syndrome (flushing and/or diarrhea) who were treatment naïve or stable on another somatostatin analog and who were randomized 1:1 to receive lanreotide injection 120 mg (n=59) or placebo (n=56) by deep subcutaneous injection every 4 weeks. Patients were instructed to self-administer a short-acting somatostatin analog (octreotide) as rescue medication as needed for symptom control. The use of rescue therapy and the severity and frequency of diarrhea and flushing symptoms were reported daily in electronic patient diaries. During the 16 week double-blind phase, the primary efficacy outcome measure was the percentage of days in which patients administered at least one injection of rescue medication for symptom control. Average daily frequencies of diarrhea and flushing events were assessed secondarily.

The patient population had a mean age of 59 years (range 27 to 85 years), 58% were female and 77% were White. Patients in the lanreotide arm experienced 15% fewer days on rescue medication compared to patients in the placebo arm (34% vs. 49% of days, respectively; p=0.02). The average daily frequencies of diarrhea and flushing events in patients treated with lanreotide (and rescue medication) were numerically lower relative to patients treated with placebo (and rescue medication), but were not statistically significantly different via hierarchical testing.

16 HOW SUPPLIED/STORAGE AND HANDLING

Lanreotide Injection is supplied in strengths of 60 mg/0.2 mL, 90 mg/0.3 mL, and 120 mg/0.5 mL lanreotide as a white to pale yellow, semi-solid formulation in a single-dose, sterile, prefilled, ready-to-use, polypropylene syringe and a safety needle device. The safety needle device is a sterile, single use needle system consisting of a needle (1.2 mm x 20 mm, stainless steel) held in protective plastic safety housing.

The single-dose prefilled syringe is contained in a plastic tray and is packed in a triple-layered aluminium pouch. The sterile safety needle is co-packaged along with the sealed aluminium pouch in the kit carton box and is attached to the former at the point of use.

NDC 69097-880-67 60 mg/0.2 mL lanreotide, sterile, prefilled syringe

NDC 69097-890-67 90 mg/0.3 mL lanreotide, sterile, prefilled syringe

NDC 69097-870-67 120 mg/0.5 mL lanreotide, sterile, prefilled syringe

Storage and Handling

Store Lanreotide Injection in the refrigerator at 2°C to 8°C (36°F to 46°F). Protect from light.

Store in the original package.

Product left in its sealed pouch at room temperature (not to exceed 104°F or 40°C) for up to 72 hours may be returned to the refrigerator for continued storage and usage at a later time.

17 PATIENT COUNSELING INFORMATION

Advise the patient to read the FDA-approved patient labeling (Patient Information).

Hypersensitivity Reactions

Advise patients to immediately contact their healthcare provider if they experience serious hypersensitivity reactions, such as angioedema or anaphylaxis [see Contraindications (4)].

Cholelithiasis and Complications of Cholelithiasis

Advise patients to contact their healthcare provider if they experience signs or symptoms of gallstones (cholelithiasis) or complications of gallstones (e.g., cholecystitis, cholangitis, or pancreatitis) [see Warnings and Precautions (5.1)].

Hyperglycemia and Hypoglycemia

Advise patients to immediately contact their healthcare provider if they experience signs or symptoms of hyper- or hypoglycemia [see Warnings and Precautions (5.2)].

Cardiovascular Abnormalities

Advise patients to immediately contact their healthcare provider if they experience bradycardia [see Warnings and Precautions (5.3)].

Thyroid Function Abnormalities

Advise patients to contact their healthcare provider if they experience signs or symptoms of hypothyroidism [see Warnings and Precautions (5.4)].

Laboratory Tests

Advise patients with acromegaly that response to Lanreotide Injection should be monitored by periodic measurements of GH and IGF-1 levels, with a goal of decreasing these levels to the normal range [see Dosage and Administration (2.1)].

Steatorrhea and Malabsorption of Dietary Fats

Advise patients to contact their healthcare provider if they experience new or worsening symptoms of steatorrhea, stool discoloration, loose stools, abdominal bloating, and weight loss [see Warnings and Precautions (5.6)].

Lactation

Advise women not to breastfeed during treatment with Lanreotide Injection and for 6 months after the last dose [see Use in Specific Populations (8.2)].

Infertility

Advise females of reproductive potential of the potential for reduced fertility from Lanreotide Injection [see Use in Specific Populations (8.3)].

Manufactured by:
Pharmathen International S.A.
Industrial Park Sapes,
Rodopi Prefecture, Block No 5,
Rodopi 69300,
Greece

Manufactured for:
Cipla USA Inc.
10 Independence Boulevard, Suite 300
Warren, NJ 07059

PATIENT INFORMATION

Lanreotide (lan-REE-oh-tide) Injection
for subcutaneous use

Read this Patient Information before you receive your first Lanreotide injection and before each injection. There may be new information. This information does not take the place of talking with your healthcare provider about your medical condition or your treatment.

What is Lanreotide injection?

Lanreotide injection is a prescription medicine used for:

- the long-term treatment of people with acromegaly when:

⚬ surgery or radiotherapy have not worked well enough or

⚬ they are not able to have surgery or radiotherapy.

- the treatment of adults with a type of cancer known as neuroendocrine tumors, from the gastrointestinal tract or the pancreas (GEP-NETs) that has spread or cannot be removed by surgery.
- the treatment of adults with carcinoid syndrome to reduce the need for the use of short-acting somatostatin medicine

It is not known if Lanreotide injection is safe and effective in children.

Who should not receive Lanreotide injection?

Do not receive Lanreotide injection if you are allergic to lanreotide.

What should I tell my healthcare provider before receiving Lanreotide injection?

Before you receive Lanreotide injection, tell your healthcare provider about all of your medical conditions, including if you:

- have gallbladder problems.
- have diabetes.
- have heart problems.
- have thyroid problems.
- have kidney problems.
- have liver problems.
- are pregnant or plan to become pregnant. It is not known if Lanreotide injection will harm your unborn baby.
- are breastfeeding or plan to breastfeed. It is not known if Lanreotide injection passes into your breast milk. You should not breastfeed if you receive Lanreotide injection and for 6 months after your last dose of Lanreotide injection.
- are a person who can become pregnant. Lanreotide injection may affect fertility and may affect your ability to become pregnant. Talk to your healthcare provider if this is a concern for you.

Tell your healthcare provider about all the medicines you take, including prescription and over the-counter medicines, vitamins, and herbal supplements. Lanreotide injection and other medicines may affect each other, causing side effects. Lanreotide injection may affect the way other medicines work, and other medicines may affect how Lanreotide injection works. Your dose of Lanreotide injection or your other medicines may need to be changed.

Especially tell your healthcare provider if you take:

- insulin or other diabetes medicines.
- cyclosporine (Gengraf, Neoral, or Sandimmune).
- medicines that lower your heart rate such as beta blockers.

How will I receive Lanreotide injection?

- You will receive a Lanreotide injection dose every 4 weeks in your healthcare provider’s office.
- Your healthcare provider may change your dose of Lanreotide injection or the length of time between your injections. Your healthcare provider will tell you how long you need to receive Lanreotide injection.
- Lanreotide injection is injected deep under the skin of the upper outer area of your buttock. Your injection site should change (alternate) between your right and left buttock from one injection of Lanreotide injection to the next.
- During your treatment with Lanreotide injection for acromegaly, your healthcare provider may do certain blood tests to see if Lanreotide injection is working.

What should I avoid while receiving Lanreotide injection?

Lanreotide injection can cause dizziness. If you have dizziness, do not drive a car or operate machinery.

What are the possible side effects of Lanreotide injection?

Lanreotide injection may cause serious side effects, including:

- Gallstones (cholelithiasis) and complications that can happen if you have gallstones. Gallstones are a serious but common side effect in people who take Lanreotide injection and have acromegaly and GEP-NET. Your healthcare provider may check your gallbladder before and during treatment with Lanreotide injection. Possible complications of gallstones include inflammation and infection of the gallbladder and pancreatitis. Tell your healthcare provider if you get any symptoms of gallstones, including:

⚬ sudden pain in your upper right stomach area (abdomen)
⚬ yellowing of your skin and whites of your eyes
⚬ nausea

⚬ sudden pain in your right shoulder between your shoulder blades
⚬ fever with chills

- Changes in your blood sugar (high blood sugar or low blood sugar). If you have diabetes, test your blood sugar as your healthcare provider tells you to. Your healthcare provider may change your dose of diabetes medicine especially when you first start receiving Lanreotide injection or if your dose of Lanreotide injection changes. High blood sugar is a common side effect in people with GEP-NET.

Tell your healthcare provider right away if you have any signs or symptoms of high blood sugar or low blood sugar.

Signs and symptoms of high blood sugar may include:

⚬ increased thirst
⚬ increased appetite
⚬ nausea

⚬ weakness or tiredness
⚬ urinating more often than normal
⚬ your breath smells like fruit

Signs and symptoms of low blood sugar may include:

⚬ dizziness or lightheadedness
⚬ sweating
⚬ confusion
⚬ headache

⚬ blurred vision
⚬ slurred speech
⚬ shakiness

⚬ fast heartbeat
⚬ irritability or mood changes
⚬ hunger

- Slow heart rate. Tell your healthcare provider right away if you have slowing of your heart rate or if you have symptoms of a slow heart rate, including:

⚬ dizziness or lightheadedness
⚬ fainting or near-fainting

⚬ chest pain
⚬ shortness of breath

⚬ confusion or memory
⚬ weakness, extreme tiredness

- High blood pressure. High blood pressure can happen in people who receive Lanreotide injection and is a common side effect in people with GEP-NET.
- Changes in thyroid function. Lanreotide injection can cause the thyroid gland to not make enough thyroid hormones that the body needs (hypothyroidism) in people who have acromegaly. Tell your healthcare provider if you have signs and symptoms of low thyroid hormones levels, including:

⚬ fatigue
⚬ weight gain
⚬ a puffy face

⚬ being cold all of the time
⚬ constipation
⚬ dry skin

⚬ thinning, dry hair
⚬ decreased sweating
⚬ depression

- Fatty stool. Lanreotide injection may cause your body to have issues absorbing dietary fats. Tell your healthcare provider if you have any new or worsening symptoms including fatty or oily stools, changes in the color of your stools, loose stools, stomach (abdominal) bloating or weight loss.

The most common side effects of Lanreotide injection in people with acromegaly include:

• diarrhea
• stomach area (abdominal) pain

• nausea
• pain, itching, or a lump at the injection site

The most common side effects of Lanreotide injection in people with GEP-NET include:

• stomach area (abdominal) pain
• muscle and joint aches
• vomiting

• headache
• pain, itching, or a lump at the injection site

The most common side effects of Lanreotide Injection in people with carcinoid syndrome include:

• headache • dizziness • muscle spasm

Tell your healthcare provider right away if you have signs of an allergic reaction after receiving Lanreotide injection, including:

• swelling of your face, lips, mouth or tongue
• breathing problems
• fainting, dizziness, feeling lightheaded (low blood pressure)
• itching

• flushing or redness of your skin
• rash
• hives

These are not all the possible side effects of Lanreotide injection. Call your doctor for medical advice about side effects. You may report side effects to FDA at 1-800-FDA-1088.

General information about the safe and effective use of Lanreotide injection.

Medicines are sometimes prescribed for purposes other than those listed in a Patient Information leaflet. Do not receive Lanreotide injection for a condition for which it was not prescribed. You can ask your healthcare provider for information about Lanreotide injection that is written for health professionals.

What are the ingredients in Lanreotide injection?

Active ingredient: lanreotide acetate

Inactive ingredients: water for injection and acetic acid (for pH adjustment)

Manufactured by: Pharmathen International S.A., Rodopi, Greece

Manufactured for: Cipla USA, Inc., 10 Independence Boulevard, Suite 300, Warren, NJ 07059

SAP Code: 99353071

For more information, go to www.ciplausa.com or call 1-886-604-3268.

This Patient Information has been approved by the U.S. Food and Drug Administration.

Revised: 09/2024

PRINCIPAL DISPLAY PANEL - 60 mg/0.2 mL Carton Label

NDC 69097-880-67 Rx Only

Lanreotide Injection

60 mg*/0.2 mL

For deep subcutaneous injection

Single dose only. Discard unused portion.

Lanreotide Injection should be administered by a healthcare professional.

Leave at room temperature for 30 minutes before administration.

CONTENTS: This box contains one (1) pre-filled syringe and one (1) safety needle.

Cipla

PRINCIPAL DISPLAY PANEL - 90 mg/0.3 mL Carton Label

NDC 69097-890-67 Rx Only

Lanreotide Injection

90 mg*/0.3 mL

For deep subcutaneous injection

Single dose only. Discard unused portion.

Lanreotide Injection should be administered by a healthcare professional.

Leave at room temperature for 30 minutes before administration.

CONTENTS: This box contains one (1) pre-filled syringe and one (1) safety needle.

Cipla

PRINCIPAL DISPLAY PANEL - 120 mg/0.5 mL Carton Label

NDC 69097-870-67 Rx Only

Lanreotide Injection

120 mg*/0.5 mL

For deep subcutaneous injection

Single dose only. Discard unused portion.

Lanreotide Injection should be administered by a healthcare professional.

Leave at room temperature for 30 minutes before administration.

CONTENTS: This box contains one (1) pre-filled syringe and one (1) safety needle.

Cipla